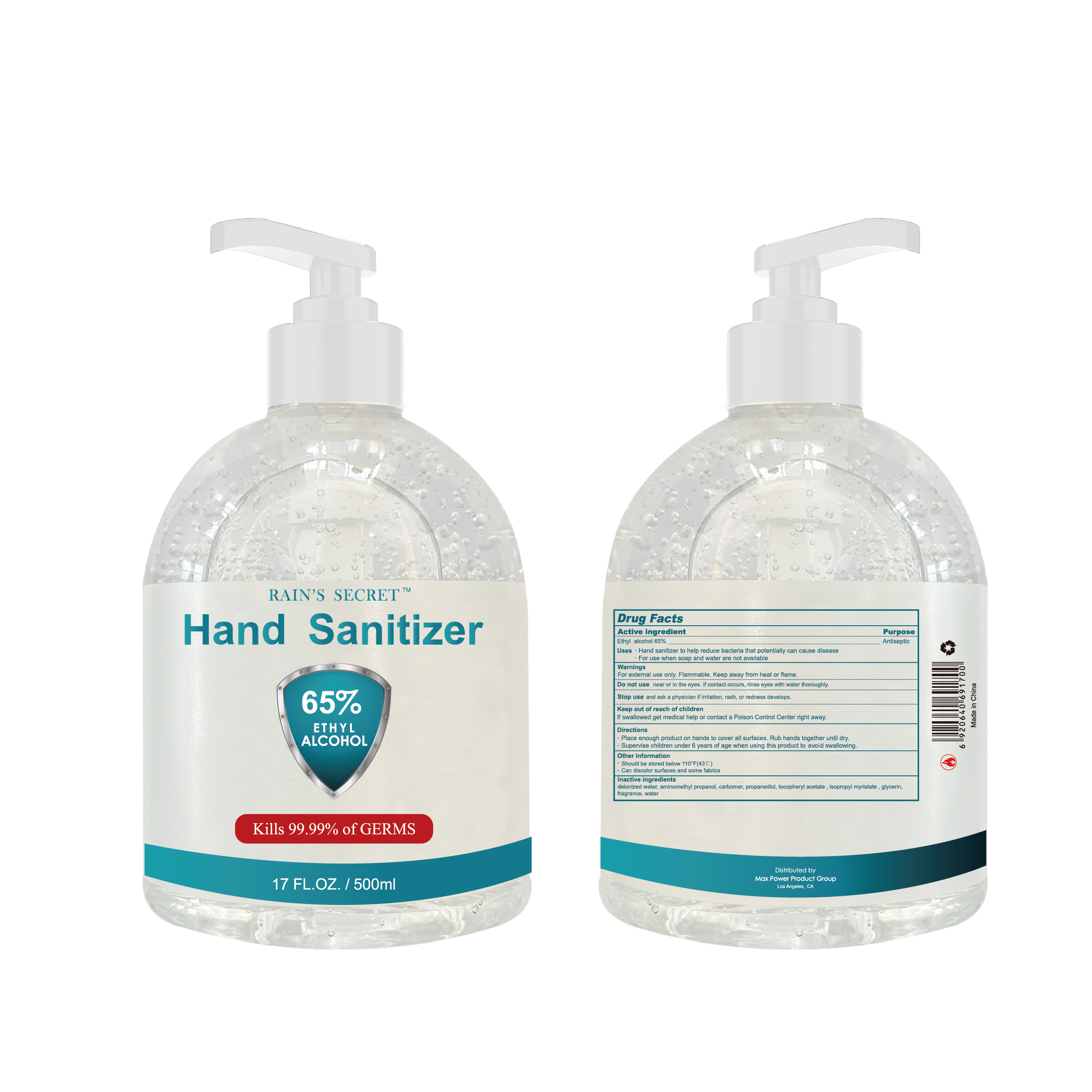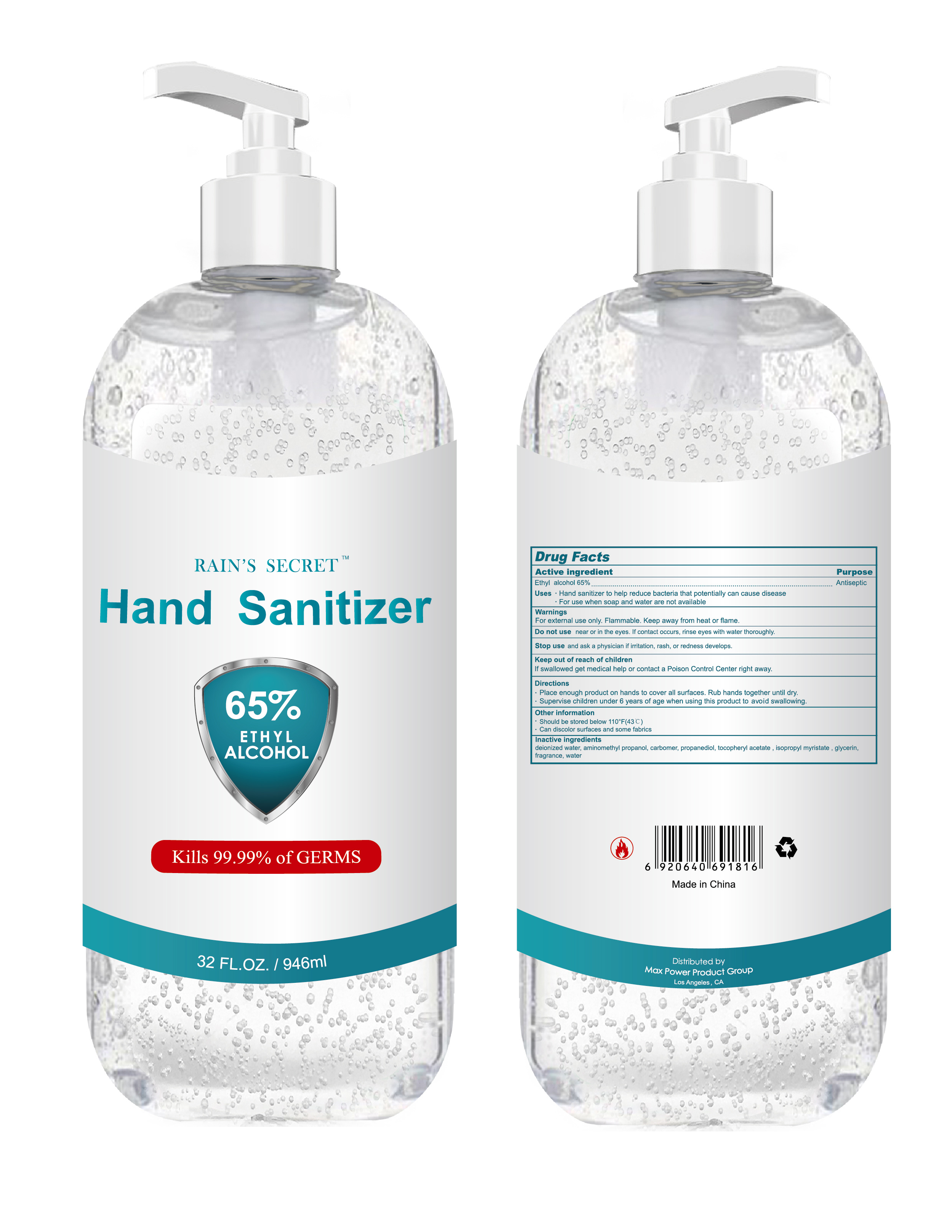 DRUG LABEL: Hand Sanitizer
NDC: 75328-002 | Form: GEL
Manufacturer: CROWN (YANGZHOU) HEALTH & BEAUTY CO., LTD
Category: otc | Type: HUMAN OTC DRUG LABEL
Date: 20200716

ACTIVE INGREDIENTS: ALCOHOL 65 mL/100 mL
INACTIVE INGREDIENTS: .ALPHA.-TOCOPHEROL ACETATE; WATER; CARBOMER HOMOPOLYMER, UNSPECIFIED TYPE; PROPANEDIOL; GLYCERIN; AMINOMETHYLPROPANOL; ISOPROPYL MYRISTATE

ACTIVE INGREDIENT

ETHYL alcohol 65% v/v. Purpose: Antiseptic

PURPOSE

Antiseptic, Hand Sanitizer

USES

- Hand Sanitizer to help reduce bacteria that potentially can cause disease.
- For use when soap and water are not available.

WARNINGS

For external use only. Flammable. Keep away from heat or flame.

DO NOT USE

near or in the eyes. If contact occurs, rinse eyes with water throughly.

STOP USE

Stop use and ask a physician if irritation,rash, or redness develops.

KEEP OUT OF REACH OF CHILDREN

If swallowed get medical help or contact a Poison Control Center right away.

DIRECTIONS

- Place enough product on hands to cover all surfaces. Rub hands together until dry.
- Supervise children under 6 years of age when using this product to avoid swallowing.

OTHER INFORMATION

- Should be stored below 110℉(43℃)
- Can discolor surfaces and some fabrics

INACTIVE INGREDIENTS

deionized water, aminomethyl propanol, carbomer, propanediol, tocopheryl acetate, isopropyl myristate, glycerin, fragrance, water

PACKAGE LABEL - PRINCIPAL DISPLAY PANEL

500mL NDC: 75328-002-01

946mL NDC: 75328-002-02